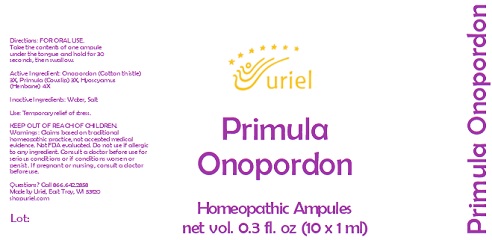 DRUG LABEL: Primula Onopordon
NDC: 48951-8398 | Form: LIQUID
Manufacturer: Uriel Pharmacy Inc.
Category: homeopathic | Type: HUMAN OTC DRUG LABEL
Date: 20231004

ACTIVE INGREDIENTS: ONOPORDUM ACANTHIUM FLOWER 3 [hp_X]/1 mL; PRIMULA VERIS FLOWER 3 [hp_X]/1 mL; HYOSCYAMUS NIGER LEAF 4 [hp_X]/1 mL
INACTIVE INGREDIENTS: WATER; SODIUM CHLORIDE

Primula Onopordon

INDICATIONS AND USAGE

Directions: FOR ORAL USE.

DOSAGE AND ADMINISTRATION

Take the contents of one ampule under the tongue and hold for 30 seconds, then swallow.

Active Ingredient: Onopordon (Cotton thistle) 3X, Primula (Cowslip) 3X, Hyoscyamus (Henbane) 4X

Inactive Ingredients: Water, Salt

PURPOSE

Use: Temporary relief of stress.

KEEP OUT OF REACH OF CHILDREN.

WARNINGS

Warnings: Claims based on traditional homeopathic practice, not accepted medical evidence. Not FDA evaluated. Do not use if allergic to any ingredient. Consult a doctor before use for serious conditions or if conditions worsen or persist. If pregnant or nursing, consult a doctor before use.

QUESTIONS

Questions? Call 866.642.2858 Made by Uriel, East Troy, WI 53120 shopuriel.com